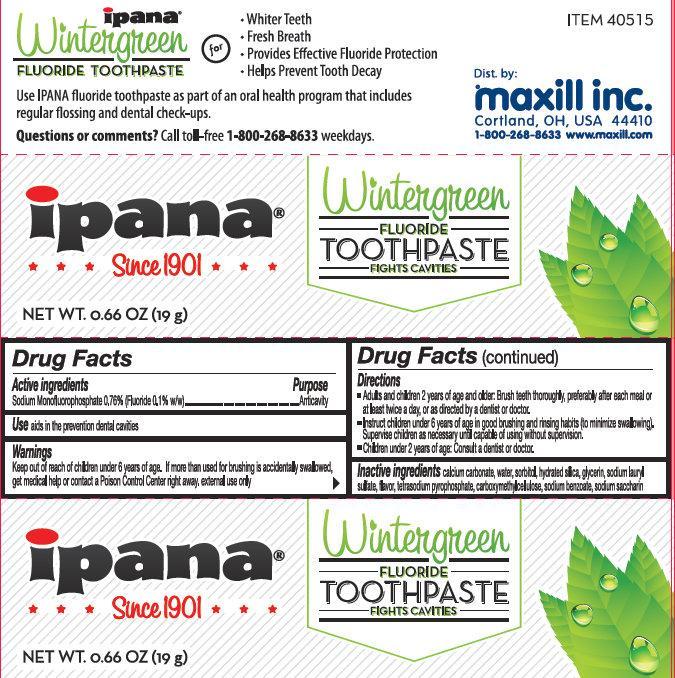 DRUG LABEL: Ipana Wintergreen Fluoride
NDC: 69510-010 | Form: PASTE
Manufacturer: Maxill Inc.
Category: otc | Type: HUMAN OTC DRUG LABEL
Date: 20250728

ACTIVE INGREDIENTS: SODIUM MONOFLUOROPHOSPHATE 0.1 g/100 g
INACTIVE INGREDIENTS: CALCIUM CARBONATE; WATER; SORBITOL; HYDRATED SILICA; GLYCERIN; SODIUM LAURYL SULFATE; SODIUM PYROPHOSPHATE; CARBOXYMETHYLCELLULOSE; SACCHARIN SODIUM; SODIUM BENZOATE

Ipana Wintergreen Fluoride

Active Ingredients

Sodium Monofluorophosphate 0.76% (Fluoride 0.1% w/w)

Purpose

Anticavity

Use

Aids in the prevention of dental cavities.

Warnings

Keep out of reach of children under 6 years of age.

If more than used for brushing is accidentaly swallowed get medical help or contact a Poison Control Center right away. external use only.

Directions

- Adults and children 2 years and older: Brush teeth thoroughly after meals or at least twice a day or use as directed by a dentist or doctor.
- Instruct children under 6 years of age in good brushing and rinsing habits (to minimize swallowing). Supervise children as necessary until capable of using without supervision.
- Children under 2 years: Consult a dentist or doctor.

Inactive Ingredients

calcium carbonate, water, sorbitol, hydrated silica, glycerin, sodium lauryl sulfate, flavor, tetrasodium pyrophosphate, carboxymethylcellulose, sodium benzoate, sodium saccharin

Product Label

ipana

Since 1901

Wintergreen

FLUORIDE

TOOTHPASTE

FIGHTS CAVITIES

NET WT. 0.66 OZ (19g)

ITEM 40515

Dist. by:

Maxill inc.

Cortland, OH, USA 44410

1-800-268-8633 www.maxill.com

Made in Malaysia